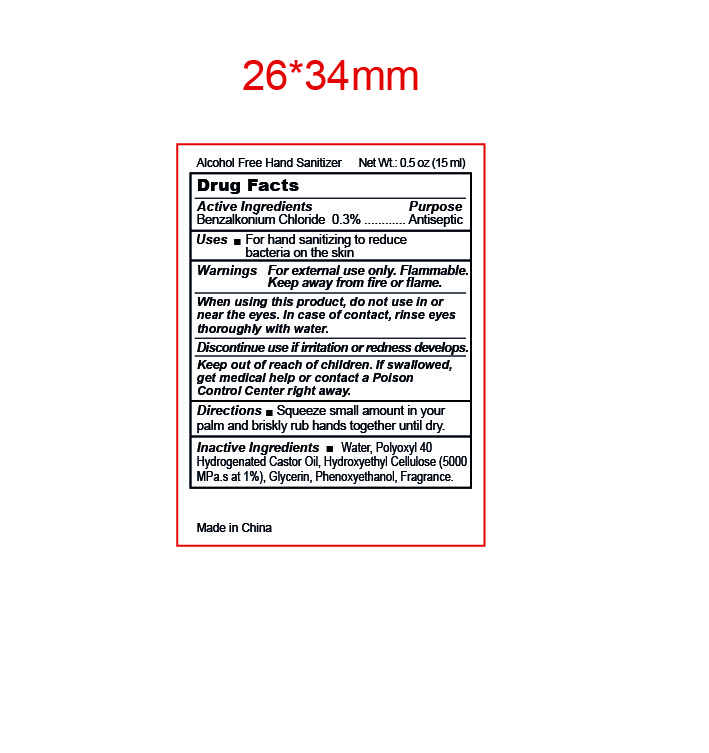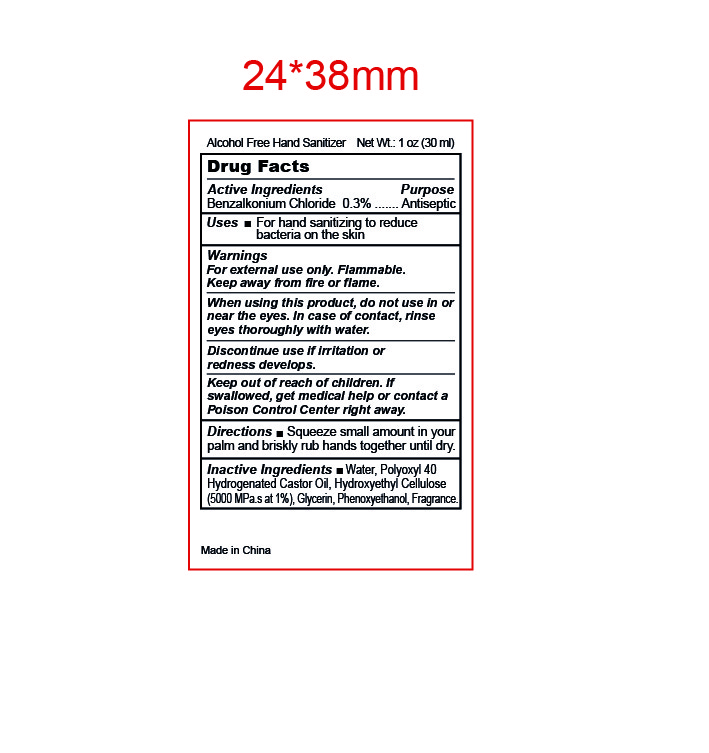 DRUG LABEL: Alcohol Free Hand Sanitizer
NDC: 87001-004 | Form: GEL
Manufacturer: HAIAN KANGRUI TEXTILE CO., LTD.
Category: otc | Type: HUMAN OTC DRUG LABEL
Date: 20250812

ACTIVE INGREDIENTS: BENZALKONIUM CHLORIDE 0.3 g/100 mL
INACTIVE INGREDIENTS: WATER; HYDROXYETHYL CELLULOSE (5000 MPA.S AT 1%); GLYCERIN; PHENOXYETHANOL; POLYOXYL 40 HYDROGENATED CASTOR OIL

87001-004

Active Ingredient

Benzalkonium Chloride 0.3%

Purpose

Antiseptic

Uses

For hand sanitizing to reduce bacteria on the skin.

Warnings

For external use only.

Flammable. Keep away from fire and flame.

When using this product，

do not use in or near the eyes.In case of contact，rinse eyes thoroughly with water.

Discontinue use

if irritation or redness develops.

Keep out of reach of children.

If swallowed, get medical help or contact a Poison Control Center right away.

Directions

Squeeze small amount in your palm and briskly rub hands together until dry.

Inactive ingredients

WATER, POLYOXYL 40 HYDROGENATED CASTOR OIL, HYDROXYETHYL CELLULOSE (5000 MPA.S AT 1%), GLYCERIN, PHENOXYETHANOL, FRAGRANCE.